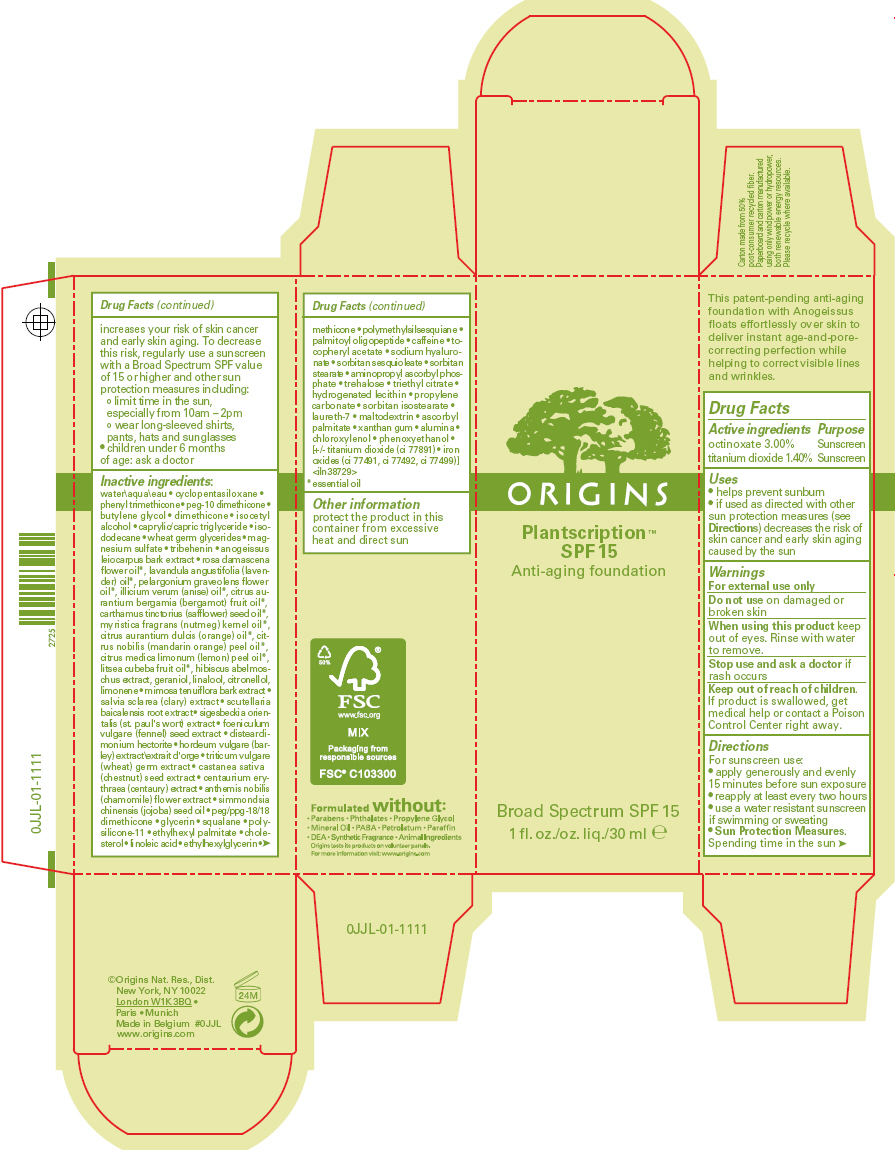 DRUG LABEL: PLANTSCRIPTION SPF 15 ANTI-AGING FOUNDATION
NDC: 59427-004 | Form: LIQUID
Manufacturer: ORIGINS NATURAL RESOURCES INC.
Category: otc | Type: HUMAN OTC DRUG LABEL
Date: 20120604

ACTIVE INGREDIENTS: OCTINOXATE 3 mL/100 mL; TITANIUM DIOXIDE 1.4 mL/100 mL
INACTIVE INGREDIENTS: water; cyclomethicone 5; phenyl trimethicone; butylene glycol; dimethicone; isocetyl alcohol; medium-chain triglycerides; isododecane; wheat germ oil; magnesium sulfate; tribehenin; anogeissus leiocarpus bark; rosa damascena flower oil; lavender oil; pelargonium graveolens flower oil; bergamot oil; safflower oil; nutmeg oil; orange oil; mandarin oil; lemon oil; litsea oil; abelmoschus moschatus seed; geraniol; linalool, (+/-)-; .beta.-citronellol, (r)-; mimosa tenuiflora bark; scutellaria baicalensis root; fennel seed; wheat germ; spanish chestnut; centaurium erythraea; chamaemelum nobile flower; jojoba oil; peg/ppg-18/18 dimethicone; glycerin; squalane; ethylhexyl palmitate; cholesterol; linoleic acid; ethylhexylglycerin; palmitoyl oligopeptide; caffeine; .alpha.-tocopherol acetate; hyaluronate sodium; sorbitan sesquioleate; sorbitan monostearate; aminopropyl ascorbyl phosphate; trehalose; triethyl citrate; propylene carbonate; sorbitan isostearate; laureth-7; maltodextrin; ascorbyl palmitate; xanthan gum; aluminum oxide; chloroxylenol; phenoxyethanol; ferric oxide red; ferric oxide yellow; ferrosoferric oxide

PLANTSCRIPTION™ SPF 15 ANTI-AGING FOUNDATION

Drug Facts

ACTIVE INGREDIENT

Active ingredients | Purpose
octinoxate 3.00% | Sunscreen
titanium dioxide 1.40% | Sunscreen

Uses

- helps prevent sunburn
- if used as directed with other sun protection measures (see Directions) decreases the risk of skin cancer and early skin aging caused by the sun

Warnings

For external use only

Do not use on damaged or broken skin

When using this product keep out of eyes. Rinse with water to remove.

Stop use and ask a doctor if rash occurs

Keep out of reach of children. If product is swallowed, get medical help or contact a Poison Control Center right away.

Directions

For sunscreen use:

- apply generously and evenly 15 minutes before sun exposure
- reapply at least every two hours
- use a water resistant sunscreen if swimming or sweating
- Sun Protection Measures. Spending time in the sun increases your risk of skin cancer and early skin aging. To decrease this risk, regularly use a sunscreen with a Broad Spectrum SPF value of 15 or higher and other sun protection measures including:
  - limit time in the sun, especially from 10am – 2pm
  - wear long-sleeved shirts, pants, hats and sunglasses
- children under 6 months of age: ask a doctor

Inactive ingredients

water\aqua\eau • cyclopentasiloxane • phenyl trimethicone • peg-10 dimethicone • butylene glycol • dimethicone • isocetyl alcohol • caprylic/capric triglyceride • isododecane • wheat germ glycerides • magnesium sulfate • tribehenin • anogeissus leiocarpus bark extract • rosa damascena flower oil [essential oil] , lavandula angustifolia (lavender) oil, pelargonium graveolens flower oil, illicium verum (anise) oil, citrus aurantium bergamia (bergamot) fruit oil, carthamus tinctorius (safflower) seed oil, myristica fragrans (nutmeg) kernel oil, citrus aurantium dulcis (orange) oil, citrus nobilis (mandarin orange) peel oil, citrus medica limonum (lemon) peel oil, litsea cubeba fruit oil, hibiscus abelmoschus extract, geraniol, linalool, citronellol, limonene • mimosa tenuiflora bark extract • salvia sclarea (clary) extract • scutellaria baicalensis root extract • sigesbeckia orientalis (st. paul's wort) extract • foeniculum vulgare (fennel) seed extract • disteardimonium hectorite • hordeum vulgare (barley) extract\extrait d'orge • triticum vulgare (wheat) germ extract • castanea sativa (chestnut) seed extract • centaurium erythraea (centaury) extract • anthemis nobilis (chamomile) flower extract • simmondsia chinensis (jojoba) seed oil • peg/ppg-18/18 dimethicone • glycerin • squalane • polysilicone-11 • ethylhexyl palmitate • cholesterol • linoleic acid • ethylhexylglycerin • methicone • polymethylsilsesquiane • palmitoyl oligopeptide • caffeine • tocopheryl acetate • sodium hyaluronate • sorbitan sesquioleate • sorbitan stearate • aminopropyl ascorbyl phosphate • trehalose • triethyl citrate • hydrogenated lecithin • propylene carbonate • sorbitan isostearate • laureth-7 • maltodextrin • ascorbyl palmitate • xanthan gum • alumina • chloroxylenol • phenoxyethanol • [+/- titanium dioxide (ci 77891) • iron oxides (ci 77491, ci 77492, ci 77499)] <iln38729>

Other information

protect the product in this container from excessive heat and direct sun

©Origins Nat. Res., Dist.
New York, NY 10022

PRINCIPAL DISPLAY PANEL - 30 ml Bottle Carton

ORIGINS

Plantscription™
SPF 15

Anti-aging foundation

Broad Spectrum SPF 15
1 fl. oz./oz. liq./30 ml e